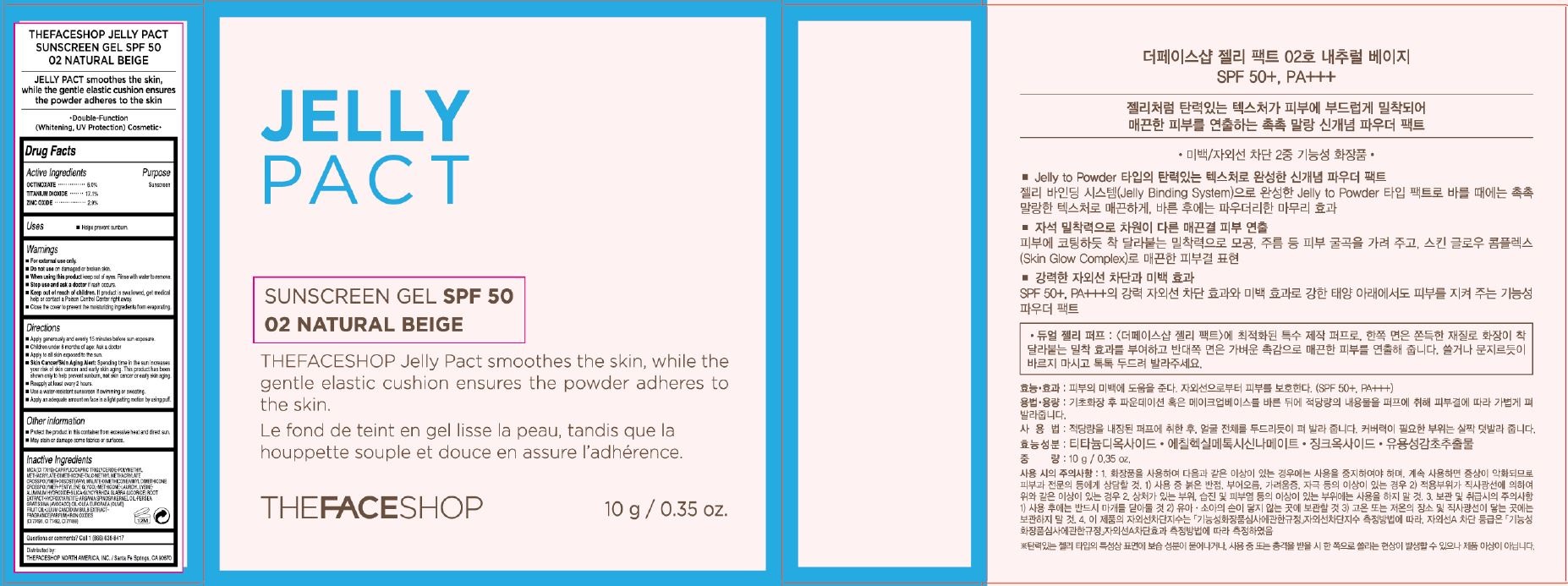 DRUG LABEL: TheFaceShop Jelly Pact
NDC: 51523-188 | Form: GEL
Manufacturer: THEFACESHOP CO., LTD.
Category: otc | Type: HUMAN OTC DRUG LABEL
Date: 20141120

ACTIVE INGREDIENTS: OCTINOXATE .6 g/10 g; TITANIUM DIOXIDE .17 g/10 g; ZINC OXIDE .29 g/10 g
INACTIVE INGREDIENTS: MICA

TheFaceShop Jelly Pact 34200188

Active Ingredients

Octinoxate 6.0 %, Titanium Dioxide 17.1, Zinc Oxide 2.9 % %,

Purpose

Sunscreen

Sunscreen

Sunscreen

Warnings

For external use only.

Do not use on damaged or broken skin

When using this product keep out of eyes. Rinse with water to remove.

Stop use and ask a doctor if rash occurs.

Keep out of reach of children. If product is swallowed, get medical help or contact a Poison Control Center right away.

Close the cover to prevent the moisturizing ingredients from evaporating.

Directions

Apply generously and evenly 15 minutes before sun exposure.
Children under 6 months of age: Ask a doctor.
Apply to all skin exposed to the sun.
Skin Cancer/Skin Aging Alert: Spending time in the sun increases your risk of skin cancer and early skin aging. This product has been shown only to help prevent sunburn, not skin cancer or early skin aging.
Reapply at least every 2 hours.
Use a water-resistant sunscreen if swimming or sweating.
Apply an adequate amount on face in a light patting motion by using puff.

Other Information

Protect the product in this container from excessive heat and direct sun

May stain or damage some fabrics or surfaces

Inactive Ingredients

Mica (CI 77019), Caprylic/Capric Triglyceride, Polymethyl Methacrylate, Dimethicone, Talc, Methyl Methacrylate Crosspolymer, Diisostearyl Malate, Dimethicone/Vinyl Dimethicone Crosspolymer, Pentylene Glycol, Methicone, Lauroyl Lysine, Aluminum Hydroxide, Silica, Glycyrrhiza Glabra (Licorice) Root Extract, Hydroxyapatite, Argania Spinosa Kernel Oil, Persea Gratissima (Avocado) Oil, Olea Europaea (Olive) Fruit Oil, Lilium Candidum Bulb Extract, Fragrance(Parfum), Iron Oxides (CI 77491, CI 77492, CI 77499)

Questions or comments? Call 1-866-638-8417

Distributed by:

THEFACESHOP NORTH AMERICA, INC.

Santa Fe Springs, CA 90670

PACKAGE LABEL

JELLY PACT

SUNSCREEN GEL SPF 50

02 NATURAL BEIGE